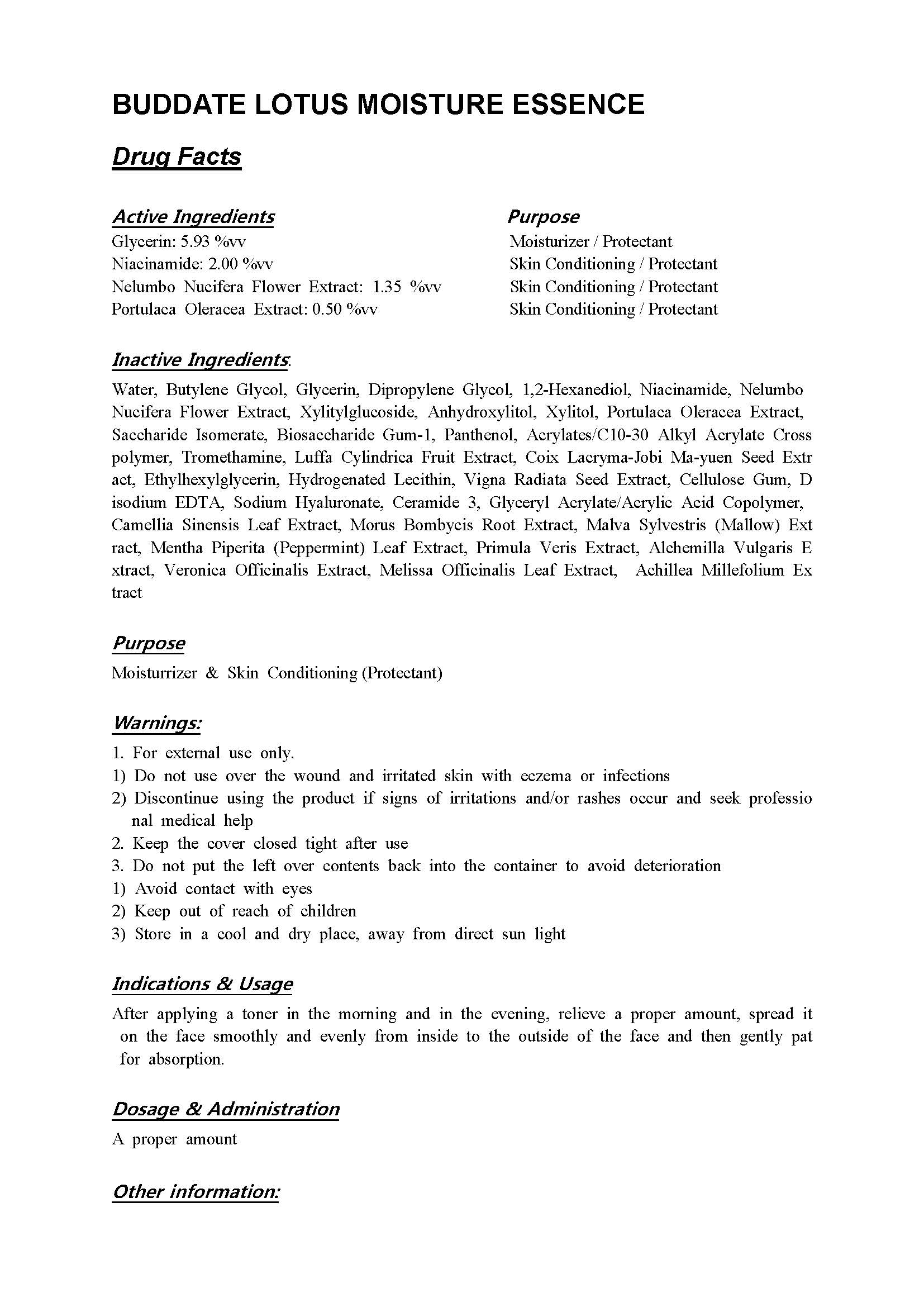 DRUG LABEL: BUDDATE LOTUS MOISTURE ESSENCE
NDC: 71173-2000 | Form: LIQUID
Manufacturer: BUDDATE Co Ltd
Category: otc | Type: HUMAN OTC DRUG LABEL
Date: 20251130

ACTIVE INGREDIENTS: PURSLANE 0.5 g/100 mL; NIACINAMIDE 2 g/100 mL; GLYCERIN 5.93 g/100 mL; NELUMBO NUCIFERA FLOWER 1.35 g/100 mL
INACTIVE INGREDIENTS: WATER; BUTYLENE GLYCOL

Drug Facts

ACTIVE INGREDIENT

Glycerin: 5.93 %vv

Niacinamide: 2.00 %vv

Nelumbo Nucifera Flower Extract: 1.35 %vv

Portulaca Oleracea Extract: 0.50 %vv

INACTIVE INGREDIENT

Water, Butylene Glycol, Glycerin, Dipropylene Glycol, 1,2-Hexanediol, Niacinamide, Nelumbo Nucifera Flower Extract, Xylitylglucoside, Anhydroxylitol, Xylitol, Portulaca Oleracea Extract, Saccharide Isomerate, Biosaccharide Gum-1, Panthenol, Acrylates/C10-30 Alkyl Acrylate Crosspolymer, Tromethamine, Luffa Cylindrica Fruit Extract, Coix Lacryma-Jobi Ma-yuen Seed Extract, Ethylhexylglycerin, Hydrogenated Lecithin, Vigna Radiata Seed Extract, Cellulose Gum, Disodium EDTA, Sodium Hyaluronate, Ceramide 3, Glyceryl Acrylate/Acrylic Acid Copolymer, Camellia Sinensis Leaf Extract, Morus Bombycis Root Extract, Malva Sylvestris (Mallow) Extract, Mentha Piperita (Peppermint) Leaf Extract, Primula Veris Extract, Alchemilla Vulgaris Extract, Veronica Officinalis Extract, Melissa Officinalis Leaf Extract, Achillea Millefolium Extract

PURPOSE

Moisturrizer & Skin Conditioning (Protectant)

keep out of reach of the children

INDICATIONS AND USAGE

After applying a toner in the morning and in the evening, relieve a proper amount, spread it on the face smoothly and evenly from inside to the outside of the face and then gently pat for absorption.

WARNINGS

1. For external use only.

1) Do not use over the wound and irritated skin with eczema or infections

2) Discontinue using the product if signs of irritations and/or rashes occur and seek professional medical help

2. Keep the cover closed tight after use

3. Do not put the left over contents back into the container to avoid deterioration

1) Avoid contact with eyes

2) Keep out of reach of children

3) Store in a cool and dry place, away from direct sun light

DOSAGE AND ADMINISTRATION

for external use only